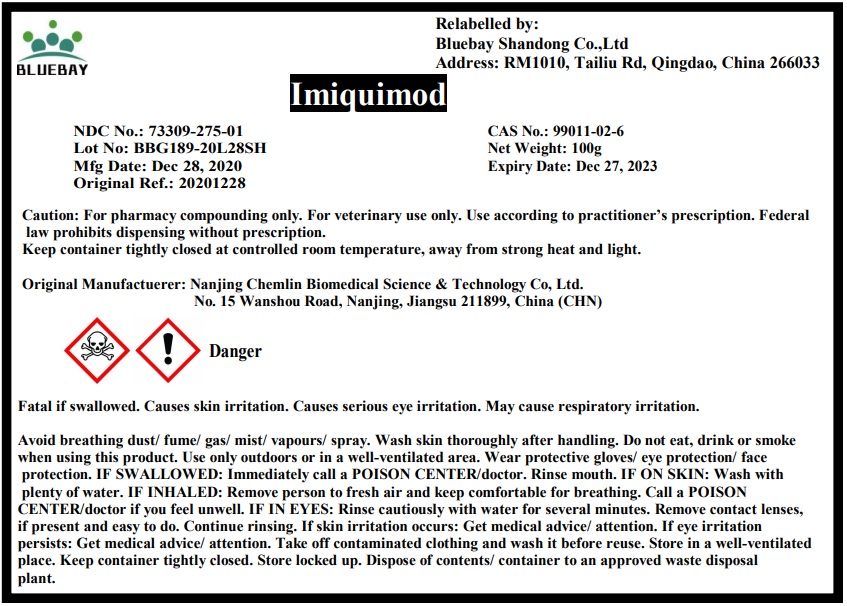 DRUG LABEL: Imiquimod
NDC: 73309-275 | Form: POWDER
Manufacturer: BLUEBAY SHANDONG CO.,LTD
Category: other | Type: BULK INGREDIENT
Date: 20210406

ACTIVE INGREDIENTS: IMIQUIMOD 1 g/1 g

Imquimod